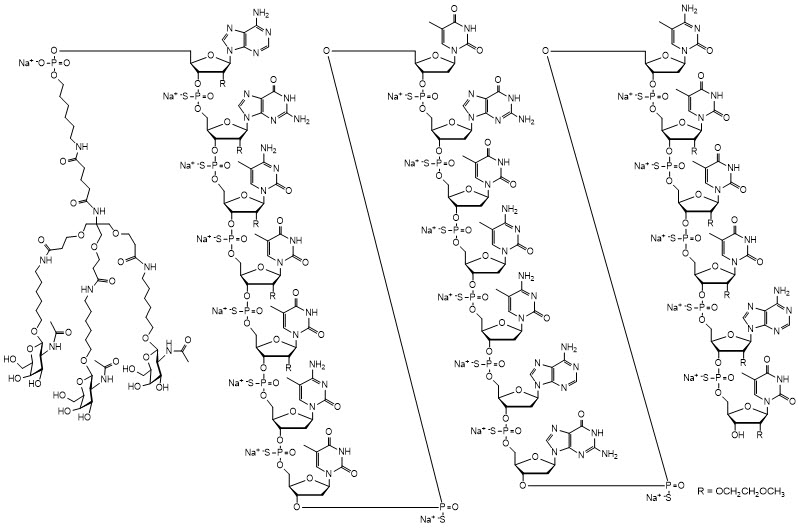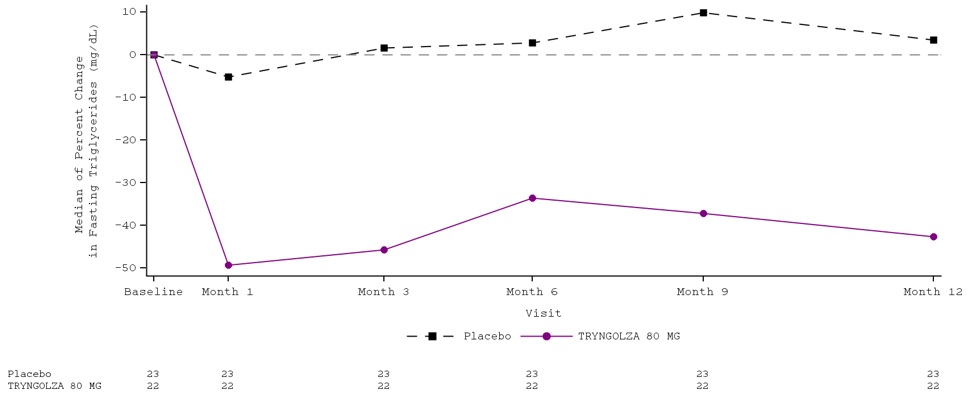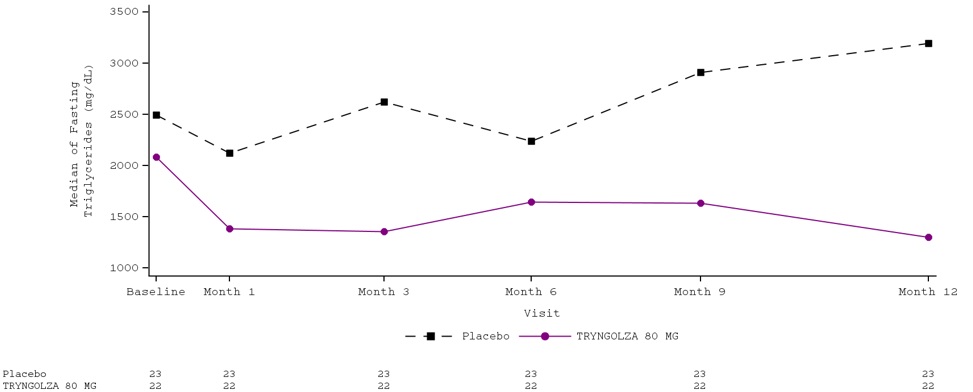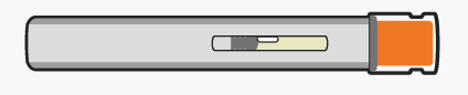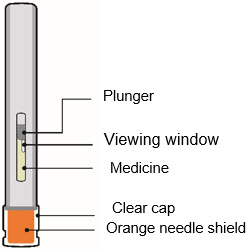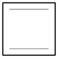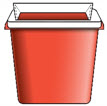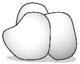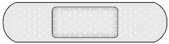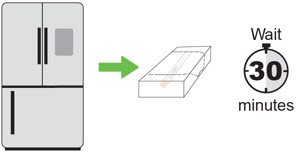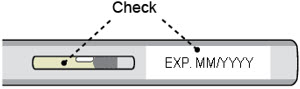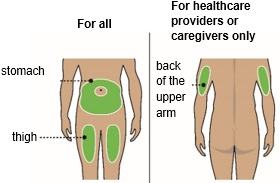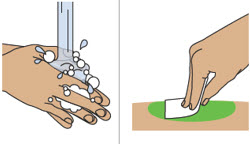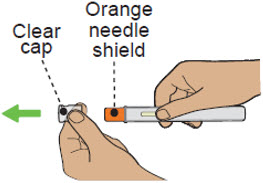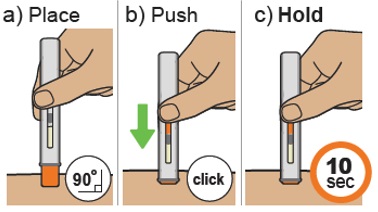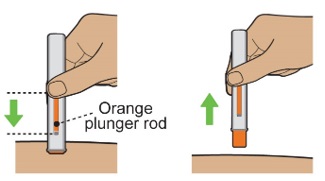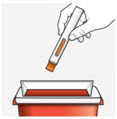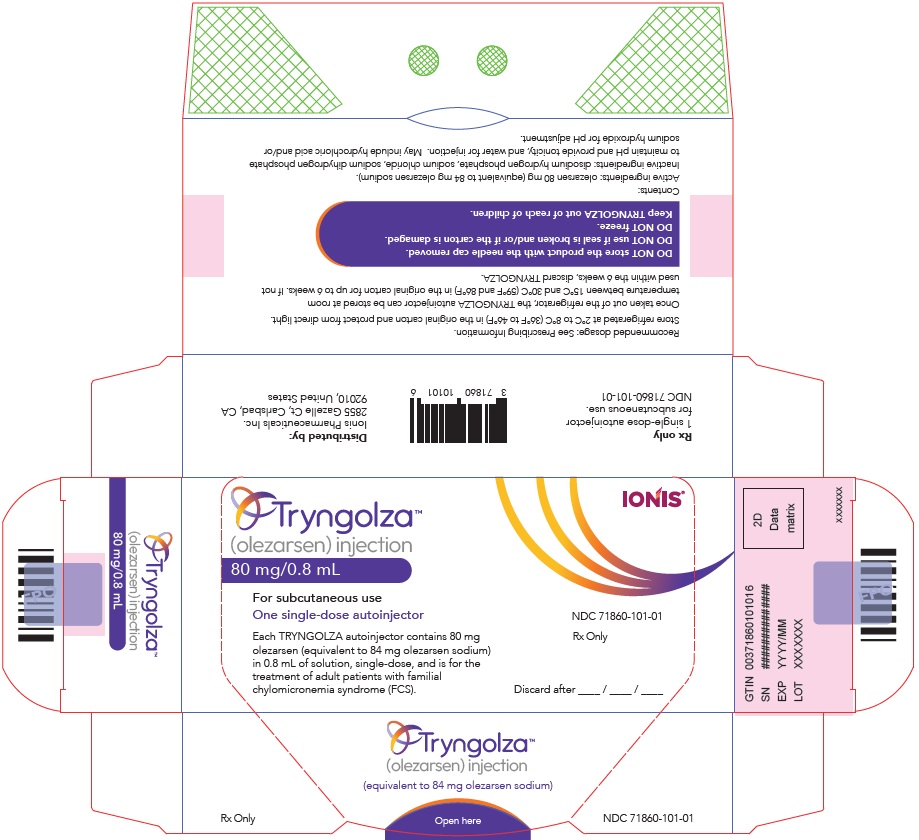 DRUG LABEL: TRYNGOLZA
NDC: 71860-101 | Form: INJECTION, SOLUTION
Manufacturer: Ionis Pharmaceuticals, Inc.
Category: prescription | Type: HUMAN PRESCRIPTION DRUG LABEL
Date: 20250131

ACTIVE INGREDIENTS: OLEZARSEN SODIUM 80 mg/0.8 mL
INACTIVE INGREDIENTS: SODIUM PHOSPHATE, DIBASIC, ANHYDROUS; SODIUM CHLORIDE; SODIUM PHOSPHATE, MONOBASIC, UNSPECIFIED FORM; WATER; HYDROCHLORIC ACID; SODIUM HYDROXIDE

HIGHLIGHTS OF PRESCRIBING INFORMATION

These highlights do not include all the information needed to use TRYNGOLZA safely and effectively. See full prescribing information for TRYNGOLZA.
TRYNGOLZA (olezarsen) injection, for subcutaneous use
Initial U.S. Approval: 2024

1 INDICATIONS AND USAGE

TRYNGOLZA is an APOC-III-directed antisense oligonucleotide (ASO) indicated as an adjunct to diet to reduce triglycerides in adults with familial chylomicronemia syndrome (FCS). (1)

2 DOSAGE AND ADMINISTRATION

- The recommended dosage of TRYNGOLZA is 80 mg administered subcutaneously once monthly. (2.1)
- Administer TRYNGOLZA into the abdomen or front of the thigh. The back of the upper arm can also be used as an injection site if a healthcare provider or caregiver administers the injection. (2.2)

3 DOSAGE FORMS AND STRENGTHS

Injection: 80 mg/0.8 mL in a single-dose autoinjector. (3)

4 CONTRAINDICATIONS

History of serious hypersensitivity reactions to olezarsen or any of the excipients in TRYNGOLZA. (4)

5 WARNINGS AND PRECAUTIONS

Hypersensitivity reactions have been reported in patients treated with olezarsen. Advise patients on the signs and symptoms of hypersensitivity reactions and instruct patients to promptly seek medical attention and discontinue use of TRYNGOLZA if hypersensitivity reactions occur. (5.1)

6 ADVERSE REACTIONS

Most common adverse reactions (incidence >5% of TRYNGOLZA-treated patients and >3% higher frequency than placebo) were injection site reactions, decreased platelet count, and arthralgia. (6.1)

To report SUSPECTED ADVERSE REACTIONS, contact Ionis Pharmaceuticals Inc. at toll free number 1-833-644-6647 or FDA at 1-800-FDA-1088 or www.fda.gov/medwatch.

FULL PRESCRIBING INFORMATION

1 INDICATIONS AND USAGE

TRYNGOLZA is indicated as an adjunct to diet to reduce triglycerides in adults with familial chylomicronemia syndrome (FCS).

2 DOSAGE AND ADMINISTRATION

2.1 Recommended Dosage

The recommended dosage of TRYNGOLZA is 80 mg administered subcutaneously once monthly [see Dosage and Administration (2.2)] .

2.2 Administration Instructions

Prior to initiation, train patients and/or caregivers on proper preparation and administration of TRYNGOLZA [see Instructions for Use] .

Remove the single-dose autoinjector from the refrigerator 30 minutes prior to the injection and allow to warm to room temperature. Do not use other warming methods.

Inspect TRYNGOLZA visually for particulate matter prior to administration. The solution should be clear and colorless to yellow. Do notuse if cloudiness, particulate matter, or discoloration is observed prior to administration.

Maintain a low-fat diet (≤20g fat per day) in conjunction with TRYNGOLZA.

Inject TRYNGOLZA subcutaneously into the abdomen or front of the thigh. The back of the upper arm can also be used as an injection site if a healthcare provider or caregiver administers the injection.

Administer TRYNGOLZA as soon as possible after a missed dose. Resume dosing at monthly intervals from the date of the most recently administered dose.

3 DOSAGE FORMS AND STRENGTHS

Injection: 80 mg/0.8 mL of olezarsen as a clear, colorless to yellow solution in a single-dose autoinjector.

4 CONTRAINDICATIONS

TRYNGOLZA is contraindicated in patients with a history of serious hypersensitivity to olezarsen or any of the excipients in TRYNGOLZA. Hypersensitivity reactions, including symptoms of bronchospasm, diffuse erythema, facial swelling, urticaria, chills, and myalgias, requiring medical treatment have occurred [see Warnings and Precautions (5.1)] .

5 WARNINGS AND PRECAUTIONS

5.1 Hypersensitivity Reactions

Hypersensitivity reactions (including symptoms of bronchospasm, diffuse erythema, facial swelling, urticaria, chills, and myalgias) have been reported in patients treated with TRYNGOLZA [see Adverse Reactions (6.1)] . Advise patients on the signs and symptoms of hypersensitivity reactions and instruct patients to promptly seek medical attention and discontinue use of TRYNGOLZA if hypersensitivity reactions occur.

6 ADVERSE REACTIONS

The following clinically significant adverse reactions are discussed elsewhere in the labeling:

- Hypersensitivity Reactions [see Warnings and Precautions (5.1)]

6.1 Clinical Trials Experience

Because clinical trials are conducted under widely varying conditions, adverse reaction rates observed in the clinical trials of TRYNGOLZA cannot be directly compared to rates in the clinical trials of another drug and may not reflect the rates observed in practice.

The safety of TRYNGOLZA was evaluated in 66 patients with FCS enrolled in Trial 1 (NCT #04568434) [see Clinical Studies (14)] . In this trial, 43 patients received at least one dose of TRYNGOLZA, 50 mg (N=21) or 80 mg (N=22) and 23 patients received placebo. TRYNGOLZA 50 mg is not an approved dosing regimen for FCS [see Dosage and Administration (2.1)]. Across treatment groups, the mean age was 45 years and 42% of patients were male. Eighty-five percent (85%) of patients were White, 9% were Asian and 6% were reported as other races; 11% identified as Hispanic or Latino ethnicity. Forty-three (43) patients were exposed to TRYNGOLZA for a median of 52 weeks; 22 patients were treated with TRYNGOLZA 80 mg every 4 weeks for a median of 52 weeks.

Adverse reactions led to discontinuation of treatment in 7% of TRYNGOLZA-treated patients and 0% of placebo-treated patients. The most common reasons for TRYNGOLZA treatment discontinuation were hypersensitivity reactions. Adverse reactions (>5% of patients treated with TRYNGOLZA and at >3% higher frequency than placebo) are presented in Table 1.

Table 1. Adverse Reactions That Occurred in >5% of Patients Treated with TRYNGOLZA and at >3% Higher Frequency than Placebo (Trial 1)

Adverse Reaction [Grouped terms composed of several similar terms] | Total TRYNGOLZA (N = 43) | Placebo (N = 23)
Injection site reactions | 8 (19%) | 2 (9%)
Decreased platelet count | 5 (12%) | 1 (4%)
Arthralgia | 4 (9%) | 0

Laboratory Tests
Decrease in Platelet Count:TRYNGOLZA can cause reductions in platelet count. In Trial 1, the mean platelet count in the TRYNGOLZA 80 mg group was 188,000 mm^3at baseline, and the mean percent change in platelet count was -10% at Week 53. In comparison, the mean platelet count in the placebo group was 215,000/mm^3at baseline, and the mean percent change in platelet count was 22% at Week 53. No TRYNGOLZA-treated patient with FCS had a platelet count <50,000/mm^3. There were no major bleeding events associated with a low platelet count. Overall, the proportion of patients experiencing a bleeding adverse event was similar across the TRYNGOLZA and placebo treatment groups.

Increase in Glucose:Small increases in average values in fasting glucose (≤17 mg/dL) and HbA1c (<0.2 percentage points) were observed over time with TRYNGOLZA treatment in the FCS population in Trial 1. The incidence of hyperglycemia (defined as adverse events, new antidiabetic medication, or laboratory values) was higher in olezarsen-treated patients without a medical history of diabetes at baseline (52%) compared to placebo-treated patients (35%).

Increase in Liver Enzymes:Increases from baseline in liver enzymes within the normal range were observed with olezarsen treatment in the FCS population. These increases occurred within the first 3 months of treatment and stabilized. Liver enzymes returned towards baseline with discontinuation of olezarsen.

Increase in LDL-cholesterol:Increases in low-density lipoprotein cholesterol (LDL-C) and total apolipoprotein B (apoB) were observed in the FCS population treated with TRYNGOLZA compared to those treated with placebo [see Clinical Studies (14)] . Despite increases in LDL-C, the maximum LDL-C value remained low for most patients (i.e., <70 mg/dL for 74% of patients treated with TRYNGOLZA).

8 USE IN SPECIFIC POPULATIONS

8.1 Pregnancy

Risk Summary

There are no available data on TRYNGOLZA use in pregnant women to inform drug-associated risk of major birth defects, miscarriage, or adverse maternal or fetal outcomes. Patients with FCS are at risk for pancreatitis during pregnancy because of defects in lipid metabolism and increased triglyceride levels (see Clinical Considerations) .

In animal reproduction studies conducted with the unconjugated antisense oligonucleotide (lacking GalNAc) in rabbits and mice, no adverse effects on development or pregnancy were observed at doses 21 times or 20 times, respectively, the maximum recommended clinical dose.

The background risk of major birth defects and miscarriage for the indicated population is unknown. All pregnancies have a background risk of birth defect, loss, or other adverse outcomes. In the U.S. general population, the estimated background risk of major birth defects and miscarriage in clinically recognized pregnancies is 2-4% and 15-20% respectively.

Clinical Considerations

Disease-Associated Maternal and/or Embryo-Fetal Risk
During pregnancy, triglyceride levels increase during the third trimester of pregnancy. In patients with underlying defects in lipid metabolism, such as FCS, severe gestational hypertriglyceridemia may occur, increasing the risk of acute pancreatitis during pregnancy.

Data

Animal Data

Olezarsen was not evaluated for potential effects on embryofetal development (EFD). However, effects of the administration of the unconjugated antisense oligonucleotide (ASO), which shares the same nucleotide sequence but lacks the N-acetyl galactosamine [GalNAc] moiety [see Description (11)] , were evaluated.

In a combined fertility and embryo-fetal development study in mice, the unconjugated ASO was administered to male and female mice by subcutaneous injection at doses of 10.5, 35, and 87.5 mg/kg/week prior to mating and through to the completion of organogenesis (gestation day 15). No adverse developmental outcomes occurred at doses up to 87.5 mg/kg/week (approximately 21-times the monthly maximum recommended human dose (MRHD) based on a body surface area (BSA) comparison of the unconjugated ASO).

In an embryo-fetal development study in pregnant rabbits, the unconjugated ASO was administered by subcutaneous injection at doses of 10.5, 21, and 52.5 mg/kg/week during the period of organogenesis (gestation days 6 to 18). No adverse developmental effects were observed at doses up to 21 mg/kg/week (approximately 20-times the monthly MRHD based on a BSA comparison of the unconjugated ASO).

In a pre-/postnatal toxicity study in mice, the unconjugated ASO was administered at 10.5, 35, or 87.5 mg/kg/week during the period of organogenesis and continuing until weaning (gestation day 6 through lactation day 21). Offspring body weights at 87.5 mg/kg/week (21-times the monthly MRHD based on BSA) were lower throughout their lives and were associated with slight delays in the attainment of morphological and developmental landmarks. No adverse effects on offspring were observed at 35 mg/kg/week (approximately 9-times the monthly MRHD based on a BSA comparison of the unconjugated ASO).

8.2 Lactation

Risk Summary

There are no data on the presence of olezarsen in either human or animal milk, the effects on the breastfed infant, or the effects on milk production. However, the unconjugated antisense ASO, which shares the same nucleotide sequence but lacks GalNAc, was present in the milk of lactating mice at low levels. When a drug is present in animal milk, it is likely that the drug will be present in human milk. Oligonucleotide-based products typically have poor oral bioavailability; therefore, it is considered unlikely that low levels present in milk will lead to clinically relevant levels in breastfed infants. The developmental and health benefits of breastfeeding should be considered along with the mother’s clinical need for TRYNGOLZA and any potential adverse effects on the breast-fed infant from TRYNGOLZA or from the underlying maternal condition.

8.4 Pediatric Use

Safety and effectiveness of TRYNGOLZA in pediatric patients have not been established.

8.5 Geriatric Use

No dose adjustment is recommended in patients aged 65 years and older [see Clinical Pharmacology (12.3)] . In clinical studies, 111 (38%) patients treated with TRYNGOLZA were ≥65 years of age. No overall differences in safety or effectiveness of TRYNGOLZA have been observed between patients 65 years of age and older and younger adult patients.

8.6 Renal Impairment

No dose adjustment is necessary in patients with mild to moderate renal impairment (estimated glomerular filtration rate [eGFR] ≥30 to <90 mL/min) [see Clinical Pharmacology (12.3)] . TRYNGOLZA has not been studied in patients with severe renal impairment or end-stage renal disease.

8.7 Hepatic Impairment

No dose adjustment is recommended in patients with mild hepatic impairment [see Clinical Pharmacology (12.3)] . TRYNGOLZA has not been studied in patients with moderate or severe hepatic impairment.

11 DESCRIPTION

Olezarsen is an ASO directed inhibitor of Apolipoprotein C-III (apoC-III) mRNA, conjugated to a ligand containing three N-acetyl galactosamine (GalNAc) residues to enable delivery of the ASO to hepatocytes.

TRYNGOLZA contains olezarsen sodium as the active ingredient. Olezarsen sodium is a white to yellow solid and it is freely soluble in water and in phosphate buffer. The molecular formula of olezarsen sodium is C296H419N71O154P20S19Na20and the molecular weight is 9124.48 daltons. The chemical name of olezarsen sodium is DNA, d(P-thio) ([2'- O-(2-methoxyethyl)] rA-[2'- O-(2-methoxyethyl)] rG-[2'- O-(2-methoxyethyl)] m5rC-[2'- O-(2-methoxyethyl)] m5rU-[2'- O-(2-methoxyethyl)] m5rU-m5C-T-T-G-T-m5C-m5C-A-G-m5C-[2'- O-(2-methoxyethyl)] m5rU-[2'- O-(2-methoxyethyl)] m5rU-[2'- O-(2-methoxyethyl)] m5rU-[2'- O-(2-methoxyethyl)] rA-[2'- O-(2-methoxyethyl)]m5rU), 5'-[26-[[2-(acetylamino)-2-deoxy-β-D-galactopyranosyl]oxy]-14,14-bis[[3-[[6-[[2-(acetylamino)-2-deoxy-β-D-galactopyranosyl]oxy]hexyl]amino]-3-oxopropoxy]methyl]-8,12,19-trioxo-16-oxa-7,13,20-triazahexacos-1-yl hydrogen phosphate], sodium salt (1:20).

The structure of olezarsen sodium is presented below:

TRYNGOLZA is a sterile, preservative-free solution for subcutaneous injection. Each single-dose autoinjector contains 80 mg olezarsen (equivalent to 84 mg of olezarsen sodium) in 0.8 mL of solution. The solution also contains the following inactive ingredients: disodium hydrogen phosphate, sodium chloride, sodium dihydrogen phosphate to maintain pH and provide tonicity, and water for injection. The solution may include hydrochloric acid and/or sodium hydroxide for pH adjustment between 6.9 to 7.9. Each dose of TRYNGOLZA injection contains 6 mg of phosphorous and 5 mg of sodium.

12 CLINICAL PHARMACOLOGY

12.1 Mechanism of Action

Olezarsen is an ASO-GalNAc3conjugate that binds to apoC-III mRNA leading to mRNA degradation and resulting in a reduction of serum apoC-III protein. Reduction of apoC-III protein leads to increased clearance of plasma TG and VLDL.

12.2 Pharmacodynamics

Fasting apoC-III
Olezarsen decreased fasting apoC-III following administration of TRYNGOLZA 80 mg dosage every 4 weeks to patients with FCS [See Clinical Studies (14)] . The placebo-corrected percent change in fasting apoC-III from baseline was -57% at 1 month, -69% at 3 months, -72% at 6 months, and -80% at 12 months.

Cardiac Electrophysiology

At a dose 1.5-times the maximum approved recommended dosage, TRYNGOLZA does not prolong the QT interval to any clinically relevant extent.

12.3 Pharmacokinetics

Olezarsen steady state mean (SD) maximum concentrations (Cmax) is 883 (662) ng/mL and area under the curve (AUCτ) is 7440 (3880) ng*h/mL at the approved recommended dosage in patients with FCS. Olezarsen Cmaxand AUC increase dose-proportionally following single subcutaneous doses ranging from 10 to 120 mg (i.e., 0.13- to 1.5-times the approved recommended dose) in healthy volunteers. No olezarsen accumulation occurs with repeat dosing.

Absorption

Olezarsen time to Cmax(Tmax) is approximately 2 hours following subcutaneous administration.

Distribution

The population estimates for the apparent central volume of distribution is 91.9 L and the apparent peripheral volume of distribution is 2960 L for olezarsen. Olezarsen is greater than 99% bound to plasma proteins, in vitro.

Olezarsen distributes primarily to the liver and kidney after subcutaneous dosing.

Elimination

Olezarsen terminal elimination half-life is approximately 4 weeks.

Metabolism

Olezarsen is metabolized by endo- and exonucleases to short oligonucleotide fragments of varying sizes within the liver.

Excretion

Less than 1% of olezarsen administered dose is eliminated unchanged in urine within 24 hours.

Specific Populations

No clinically significant differences in the pharmacokinetics of olezarsen were observed based on age (< 65 to ≥ 75 years), body weight, sex, race (White, Black or African American, Asian, Japanese, American Indian or Alaska Native, Native Hawaiian or Pacific Islander), mild-to-moderate renal impairment (eGFR ≥30 to <90 mL/min) [CKD-EPI], or mild hepatic impairment (total bilirubin ≤ ULN and AST > ULN, or total bilirubin >1 to 1.5 x ULN and any AST, National Cancer Institute Organ Dysfunction Working Group criteria). The effect of severe renal impairment (eGFR < 30 mL/min), end-stage renal disease, moderate or severe hepatic impairment (total bilirubin > 1.5 x ULN with any AST) on olezarsen pharmacokinetics is unknown.

Drug Interaction Studies

In Vitro Studies
CYP450 Enzymes:Olezarsen is not an inhibitor or inducer of CYP450 enzymes.

Transporter Systems: Olezarsen is not a substrate or inhibitor of OAT1, OAT3, OCT1, OCT2, OATP1B1, OATP1B3, MATE1, MATE2-K, BCRP, P-gp, and BSEP.

Protein Binding:Olezarsen does not displace warfarin and ibuprofen from plasma protein binding sites.

12.6 Immunogenicity

The observed incidence of anti-drug antibodies (ADAs) is highly dependent on the sensitivity and specificity of the assay. Differences in assay methods preclude meaningful comparisons of the incidence of ADAs in the study described below with the incidence of anti-drug antibodies in other studies, including those of olezarsen.

In Trial 1, with duration of treatment up to 53 weeks, 18 out of 43 (42%) patients treated with TRYNGOLZA developed treatment-emergent ADAs. The presence of ADAs did not affect olezarsen plasma Cmax, but increased Ctrough. Although ADA development was not found to affect the pharmacodynamics, safety, or efficacy of TRYNGOLZA in these patients, the available data are limited to make definitive conclusions.

13 NONCLINICAL TOXICOLOGY

13.1 Carcinogenesis, Mutagenesis, Impairment of Fertility

Carcinogenesis

No long-term carcinogenicity studies were conducted with olezarsen in animals. However, the unconjugated antisense oligonucleotide (ASO) lacking GalNAc was administered weekly in mice and rats at subcutaneous doses of 0, 6, 25 and 40 mg/kg/week (along with a mouse-specific surrogate ASO at 25 mg/kg/week) and 0, 0.2, 1 and 5 mg/kg/week, respectively, for 2 years. In male mice, there were statistically significant increases in the incidences of hepatocellular adenomas and carcinomas at ≥25 mg/kg/week and hemangiomas and hemangiosarcomas at all doses. In female mice, there were statistically significant increases in the incidences of histiocytic sarcomas at all doses (including the mouse-specific surrogate) and pituitary gland adenomas at 25 mg/kg/week. In rats, the incidence of malignant fibrous histiocytoma at the injection site was increased in both sexes at doses ≥1 mg/kg/week. These tumors are considered a response to chronic tissue irritation and inflammation caused by repeated subcutaneous injection. The clinical significance of these findings is uncertain.

Mutagenesis

Olezarsen was negative for genotoxicity in vitro (bacterial reverse mutation assay and chromosome aberration assay in Chinese hamster lung cells) and in vivo (mouse bone marrow micronucleus assay).

Impairment of Fertility

Olezarsen was administered at doses of 0, 5, 10, or 20 mg/kg given every other week to male and female mice prior to mating, followed by every other day dosing after mating and until gestation day 6 in females. There was no effect on fertility in mice administered olezarsen at doses up to 20 mg/kg (approximately 2-times the monthly maximum recommended human dose based on body surface area).

14 CLINICAL STUDIES

-The efficacy of TRYNGOLZA was demonstrated in a randomized, placebo-controlled, double-blind clinical trial in adult patients with genetically identified FCS and fasting triglyceride (TG) levels ≥880 mg/dL (Trial 1; NCT04568434). After a ≥4-week run-in period where patients continued to follow a low-fat diet with ≤20 grams fat per day, patients were randomly assigned to receive doses every 4 weeks of TRYNGOLZA 80 mg (n=22) or matching volume of placebo (n=23) via subcutaneous injection over a 53-week treatment period.

Patient demographic and baseline characteristics were generally similar across the treatment groups [see Adverse Reactions (6.1)] . The proportion of patients with diabetes at enrollment was 32% in the TRYNGOLZA 80 mg group compared with 26% in the placebo group. Patients in the TRYNGOLZA 80 mg and placebo groups were treated with statins (27%), omega-3 fatty acids (42%), fibrates (49%), or other lipid lowering therapies (13%) at study entry. Seventy-one percent (71%) of patients in the TRYNGOLZA 80 mg and placebo groups combined had a history of documented acute pancreatitis in the prior 10 years. Mean (SD) and median fasting TG levels at baseline were 2,604 (1,364) mg/dL and 2,303 mg/dL, respectively (range of 334 to 6,898 mg/dL).

The primary endpoint was percent change in fasting triglycerides from baseline to Month 6 (average of Weeks 23, 25, and 27) compared to placebo. The difference between TRYNGOLZA 80 mg group and the placebo group in percent change in fasting triglycerides from baseline to Month 6 was -42.5% (95% CI: -74.1%, -10.9%; p=0.0084). For additional results see Table 2.

Table 2. Mean Baseline (BL) and Mean Percent (%) Changes from Baseline in Lipid/ Lipoprotein Parameters in Patients with FCS at Month 6 in Trial 1

Abbreviations: apoB = apolipoprotein B; non-HDL-C = non high-density lipoprotein cholesterol; LDL-C = low-density lipoprotein cholesterol.
Note: Analyses results were based on an analysis of covariance model with treatment, the two randomization stratification factors, prior history of pancreatitis within 10 years prior to Screening (yes vs. no), previous treatment with the unconjugated ASO (yes vs. no) as the fixed effects and log-transformed Baseline value as a covariate. Missing data was imputed using placebo washout imputation. The 95% CIs of treatment differences were calculated using a robust variance estimator. For triglycerides and non-HDL, a test of residual normality did not indicate significant departure from normal distribution.
Parameter (mg/dL) | TRYNGOLZA 80 mg N = 22 |  | Placebo N = 23 |  | TRYNGOLZA 80 mg vs. Placebo
Parameter (mg/dL) | BL | % change Month 6 | BL | % change Month 6 | Treatment Difference; % change (95% CI) at Month 6
Triglycerides | 2613.1 | -30 | 2595.7 | +12 | -42.5 [Reached statistical significance (p value < 0.05).] (-74.1, -10.9)
Non-HDL-C | 262.9 | -18 | 271.3 | +5.7 | -23.4 (-45.3, -1.5)
LDL-C | 22.8 | +64 | 16.7 | +9 | +55.0 [Mean LDL-C levels increased but remained within normal range (i.e., <70 mg/dL for 74% of patients treated with TRYNGOLZA).] (0.7, 109.4)
Total ApoB | 58.4 | +20 | 59.7 | +9 | +11.7 (-12.6, 35.9)
ApoB-48 | 11.6 | -51 | 14.2 | +25 | -75.9 (-149.8, -2.0)

Median percent change from baseline (Figure 1) and median absolute TG values (Figure 2) over time demonstrated a consistent lowering effect during the 12-month treatment period.

Figure 1. Percent Change in Fasting Triglyceride (mg/dL) Over Time

Figure 2. Fasting Triglyceride (mg/dL) Over Time

Over the 12-month treatment period, the numerical incidence of acute pancreatitis in patients treated with TRYNGOLZA 80 mg was lower compared with placebo [1 (5%) patient in the TRYNGOLZA 80 mg group compared with 7 (30%) patients in the placebo group]; all of these patients had a prior history of pancreatitis within 10 years prior to screening.

16 HOW SUPPLIED/STORAGE AND HANDLING

16.1 How Supplied

TRYNGOLZA injection is a sterile, preservative-free, clear, colorless to yellow solution supplied in a single-dose autoinjector. Each autoinjector of TRYNGOLZA is filled to deliver 0.8 mL of solution containing 80 mg of olezarsen.

TRYNGOLZA is available in cartons containing one 80 mg single-dose autoinjector each (NDC 71860-101-01).

16.2 Storage and Handling

Store the TRYNGOLZA autoinjector in the refrigerator between 2°C and 8°C (36°F and 46°F) in the original carton.

Once taken out of the refrigerator, the TRYNGOLZA autoinjector can be stored at room temperature between 15°C and 30°C (59°F and 86°F) in the original carton for up to 6 weeks. If not used within the 6 weeks stored at room temperature, discard TRYNGOLZA.

Do notfreeze. Do notexpose to heat .Protect from light.

17 PATIENT COUNSELING INFORMATION

Advise the patient to read the FDA-approved patient labeling (Patient Information and Instructions for Use).

Hypersensitivity

Inform patients that serious hypersensitivity reactions, including bronchospasm, diffuse erythema, facial swelling, urticaria, chills, and myalgia, have been reported in patients treated with TRYNGOLZA. Advise patients on the signs and symptoms of hypersensitivity reactions and instruct them to stop taking TRYNGOLZA and seek medical advice promptly if such symptoms occur [see Warnings and Precautions (5.1)] .

Adherence to Diet

Advise patients with FCS that use of lipid-regulating agents does not reduce the importance of adhering to a low-fat diet [see Dosage and Administration (2)] .

Missed Dose

Instruct patients to take TRYNGOLZA as prescribed. If a dose is missed, instruct patients to take it as soon as they remember. Resume dosing at monthly intervals from the date of the most recently administered dose [see Dosage and Administration (2.1)] .

Distributed by: Ionis Pharmaceuticals Inc., Carlsbad, CA 92010

TRYNGOLZA is a trademark of Ionis Pharmaceuticals Inc. All other trademarks are the property of their respective owners.

© 2024 IONIS Pharmaceuticals Inc.

PATIENT INFORMATION
TRYNGOLZA ™ [trin-GOLE-zah]
(olezarsen)
injection, for subcutaneous use

What is TRYNGOLZA?

TRYNGOLZA is a prescription medicine used along with diet to reduce triglycerides (fat in the blood) in the treatment of adults with a condition that keeps the body from breaking down fats called familial chylomicronemia syndrome (FCS).

It is not known if TRYNGOLZA is safe and effective in children.

Do not use TRYNGOLZA if:

- you have had a serious allergic reaction to olezarsen or any of the ingredients in TRYNGOLZA. See the end of this Patient Information for a complete list of ingredients.

Before using TRYNGOLZA, tell your healthcare provider about all of your medical conditions, including if you:

- are pregnant or plan to become pregnant. It is not known if TRYNGOLZA can harm your unborn baby. Tell your healthcare provider if you become pregnant while using TRYNGOLZA.
- are breastfeeding or plan to breastfeed. It is not known if TRYNGOLZA passes into your breast milk and if it can harm your baby. Talk to your healthcare provider about the best way to feed your baby while using TRYNGOLZA.

Tell your healthcare provider about all the medicines you take,including prescription and over-the-counter medicines, vitamins, and herbal supplements.

Know the medicines you take. Keep a list of them to show your healthcare provider and pharmacist when you get a new medicine.

How should I use TRYNGOLZA?

- Read the detailed Instructions for Usethat comes with your TRYNGOLZA single-dose autoinjector.
- Your healthcare provider will show you and/or your caregiver how to inject TRYNGOLZA the first time.
- TRYNGOLZA is injected under your skin (subcutaneous use) in your stomach area (abdomen) or the front of your upper legs (thighs). Only a healthcare provider or caregiver may give you an injection in the back of your upper arm.
- TRYNGOLZA should be injected 1 time each month.
- If you miss a dose, take the missed dose as soon as possible. Then inject TRYNGOLZA 1 month from the date of your last dose to get back on a monthly dosing schedule. If you have questions about your dosing schedule, ask your healthcare provider.
- Stay on your low-fat diet (less than 20 grams of fat each day) while using TRYNGOLZA.

What are the possible side effects of TRYNGOLZA?

- Allergic reactions: TRYNGOLZA can cause side effects including allergic reactions that may be serious. Allergic reactions can include redness of the skin, red itchy bumps (hives), swelling of the face, chills or trouble breathing. Stop taking TRYNGOLZA and call your healthcare provider or get emergency help right away if you have any of these symptoms.

The most common side effects of TRYNGOLZA include:

- Injection site reactions (such as redness or pain at the injection site)
- decreased platelet count (blood cells that help to clot blood)
- joint pain or stiffness

These are not all the possible side effects of TRYNGOLZA. Tell your healthcare provider if you have any side effect that bothers you or that does not go away while taking TRYNGOLZA. Call your doctor for medical advice about side effects. You may report side effects to the FDA at 1-800-FDA-1088.

How should I store TRYNGOLZA?

- Store TRYNGOLZA autoinjector in the refrigerator between 36°F to 46°F (2°C to 8°C) in the original carton.
- TRYNGOLZA can also be stored at room temperature between 59°F to 86°F (15°C to 30°C) in the original carton for up to 6 weeks.
- Do notlet TRYNGOLZA reach temperatures above 86°F (30°C).
- Throw awaythe TRYNGOLZA autoinjector if kept at room temperature longer than 6 weeks.
- Do notfreeze.
- Do notexpose TRYNGOLZA autoinjector to heat.
- Protect from light.
- Keep the TRYNGOLZA autoinjector in the carton until ready to use.
- Do notstore the autoinjector with the clear cap removed.

Keep TRYNGOLZA and all medicines out of the reach of children.

General information about the safe and effective use of TRYNGOLZA.

Medicines are sometimes prescribed for purposes other than those listed in a Patient Information Leaflet. Do not use TRYNGOLZA for a condition for which it was not prescribed. Do not give TRYNGOLZA to other people, even if they have the same symptoms you have. It may harm them. You can ask your pharmacist or healthcare provider for information about TRYNGOLZA that is written for health professionals.

What are the ingredients in TRYNGOLZA?

Active ingredient:olezarsen sodium.

Inactive ingredients: disodium hydrogen phosphate, sodium chloride, sodium dihydrogen phosphate to maintain pH and provide tonicity and water for injection. The solution may include hydrochloric acid and/or sodium hydroxide for pH adjustment.

Distributed by: Ionis Pharmaceuticals Inc. Carlsbad, CA 92010

TRYNGOLZA is a trademark of Ionis Pharmaceuticals Inc. All other trademarks are the property of their respective owners.

For more information, go to www.TRYNGOLZA.com or call 1-833-644-6647. If you still have questions, contact your healthcare provider.

This Patient Information has been approved by the U.S. Food and Drug Administration.

Approved: 12/2024

INSTRUCTIONS FOR USE
TRYNGOLZA ™[trin-GOLE-zah]
(olezarsen)
injection, for subcutaneous use
Single-dose autoinjector
80 mg/0.8 mL

This Instructions for Use contains information on how to inject TRYNGOLZA™using the autoinjector.

Read this Instructions for Use before you start using your TRYNGOLZA autoinjector and each time you get a refill. There may be new information.This information does not take the place of talking to your healthcare provider about your medical condition or treatment. Your healthcare provider should show you or your caregiver how to use the TRYNGOLZAautoinjector the right way. If you or your caregiver have any questions, talk to your healthcare provider.

Important information:

- TRYNGOLZAis injected under the skin (subcutaneous use) only.
- Each autoinjector contains 1 single-dose and can only be used 1 time.
- Do notremove the clear cap until you are ready to inject TRYNGOLZA(See Step 5).
- Do notshare your autoinjector with anyone.
- Do notuse if the autoinjector appears damaged.

Storage information:

- Store the autoinjector in the refrigerator between 36°F to 46°F (2°C to 8°C) in the original carton.
- TRYNGOLZA can also be stored at room temperature between 59°F to 86°F (15°C to 30°C) in the original carton for up to 6 weeks.
- Do notlet TRYNGOLZA reach temperatures above 86°F (30°C).
- Throw awaythe TRYNGOLZA autoinjector if kept at room temperature longer than 6 weeks.
- Do notfreeze.
- Do notexpose the autoinjector to heat.
- Protect from light.
- Keep the autoinjector in the carton until ready to use.
- Do notstore the autoinjector with the clear cap removed.

Keep TRYNGOLZA and all medicine out of the reach of children.

Parts of your TRYNGOLZA autoinjector

Single-dose autoinjector

Other supplies (not included)

Alcohol wipe

Sharps container

Cotton ball or gauze

Small bandage

Preparing to inject TRYNGOLZA

Step 1 Remove from the refrigerator
a) Remove the autoinjector from the refrigerator.

b) Keep the autoinjector in the original carton andlet the autoinjector come to room temperature for 30 minutes before injecting.

Do nottry to speed up the warming process using other heat sources, such as a microwave or hot water.

Step 2 Check the medicine

a)Check the expiration (EXP) date.

b)Check the medicine through the viewing window. The TRYNGOLZAmedicine should be clear and colorless to yellow. There should be no particles. It is normal to see air bubbles in the solution.

Do not use the autoinjector if the:

- clear cap is missing or not attached.
- expiration (EXP) date has passed .
- medicine looks cloudy, discolored, or has particles.
- autoinjector appears damaged.

Step 3 Choose the injection site

a)Choose an injection site on the stomach or the front of the thigh.

b)Only your healthcare provider or caregivers may choose the back of upper arm.

Do not inject:

- within 2 inches (5 cm) of the belly button (navel).
- into skin that is bruised, tender, red, or hard.
- into scars or damaged skin.

Step 4 Wash hands and clean the injection site

a)Wash your hands with soap and water.

b)Clean the injection site with an alcohol wipe in a circular motion. Let the skin air dry.

Do nottouch the cleaned skin before injecting.

Injecting TRYNGOLZA

Step 5 Remove and throw away the clear cap

a)Hold the autoinjector by the middle with the clear cap facing away from you.

b)Remove the clear cap by pulling it straight off. Do nottwist it off. The needle is inside the orange needle shield.

c)Throw away the clear cap in the trash or sharps container.

- Do notremove the clear cap until right before you inject.
- Do notrecap the autoinjector.
- Do notpush the orange needle shield against the hand or finger.

Step 6 Begin injection

a)Hold the autoinjector in 1 hand. Place the orange needle shield at a 90-degree angle against your skin. Make sure you can see the viewing window.

b)Push firmly and hold the autoinjector straight against the skin. You will hear a click as the injection starts.

You may hear a second click. This is normal. The procedure is not finished.

c)Hold the autoinjector against the skin for 10 seconds to make sure the full dose has been given.

Do notmove, turn, or change the angle of the autoinjector during the injection.

Step 7 Finish injection

a)Check that the orange plunger rod has moved down to fill the entire viewing window.

- If the orange plunger rod does not fill the viewing window, you may not have received the full dose.
- If this happens or if you have other concerns, contact your healthcare provider.

b)Remove the autoinjector by lifting it straight up. After removal from the skin, the orange needle shield locks into place and covers the needle.

c)There may be a small amount of blood or liquid where you injected. This is normal.

If needed, press a cotton ball or gauze on the area and apply a small bandage.

Do notreuse the autoinjector.

Throwing away TRYNGOLZA

Step 8 Throw away autoinjector

a)Put the used autoinjector in a sharps container right away after use.

Do notthrow away the autoinjector in your household trash.
Do notrecycle your used sharps disposal container.
Do notreuse the autoinjector or clear cap.

If you do not have an FDA-cleared sharps container, you may use a household container that is:

- made of a heavy-duty plastic,
- can be closed with a tight-fitting, puncture-resistant lid, without sharps being able to come out,
- upright and stable during use,
- leak-resistant, and
- properly labelled to warn of hazardous waste inside the container.

When your sharps disposal container is almost full, you will need to follow your community guidelines for the right way to dispose of your sharps disposal container. There may be state or local laws about how you should throw away used autoinjectors.

For more information about safe sharps disposal, and specific information about sharps disposal in the state that you live in, go to the FDA's website at: http://www.fda.gov/safesharpsdisposal.

Do notthrow away your used sharps disposal container in your household trash unless your community guidelines permit this. Do notrecycle your used sharps disposal container.

For more information, go to https://www.TRYNGOLZA.com or call 1-833-644-6647. If you still have questions, contact your healthcare provider.

Distributed by: Ionis Pharmaceuticals, Inc., Carlsbad, CA 92010

This Instructions for Use has been approved by the U.S. Food and Drug Administration.

Approved: 12/2024

PRINCIPAL DISPLAY PANEL - 80 mg/0.8 mL Autoinjector Carton

Tryngolza™
(olezarsen) injection
80 mg/0.8 mL

For subcutaneous use
One single-dose autoinjector

Each TRYNGOLZA autoinjector contains 80 mg
olezarsen (equivalent to 84 mg olezarsen sodium)
in 0.8 mL of solution, single-dose, and is for the
treatment of adult patients with familial
chylomicronemia syndrome (FCS).

IONIS®

NDC 71860-101-01

Rx Only

Discard after ____ / ____ / ____